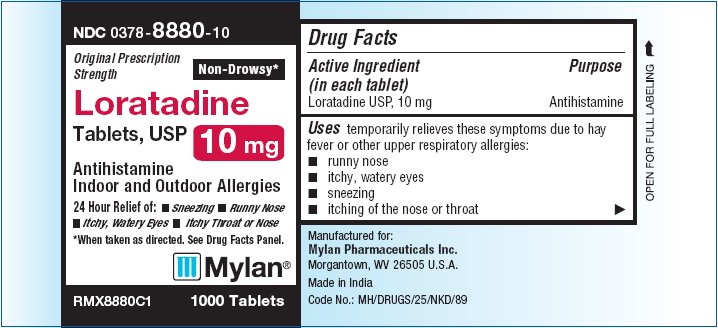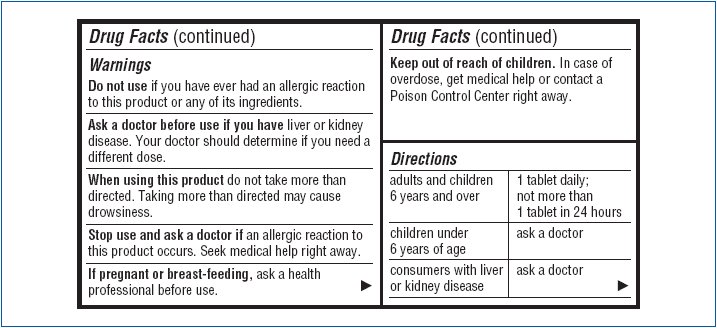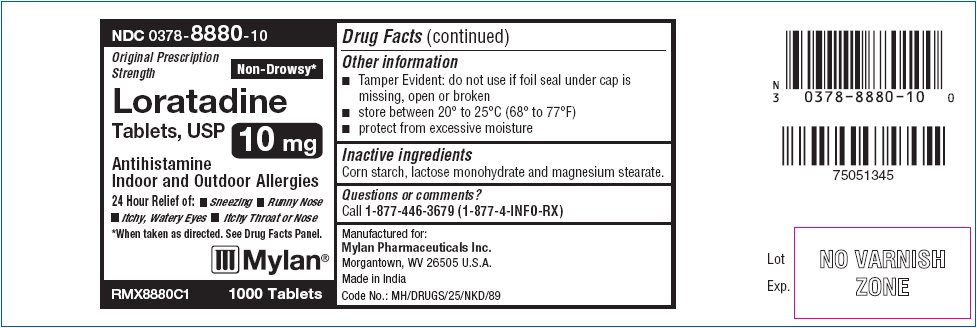 DRUG LABEL: Loratadine
NDC: 0378-8880 | Form: TABLET
Manufacturer: Mylan Pharmaceuticals Inc.
Category: otc | Type: HUMAN OTC DRUG LABEL
Date: 20131115

ACTIVE INGREDIENTS: LORATADINE 10 mg/1 1
INACTIVE INGREDIENTS: STARCH, CORN; LACTOSE MONOHYDRATE; MAGNESIUM STEARATE

Active ingredient

(in each tablet)

Loratadine USP, 10 mg

Purpose

Antihistamine

Uses

temporarily relieves these symptoms due to hay fever or other upper respiratory allergies:

- runny nose
- itchy, watery eyes
- sneezing
- itching of the nose or throat

Do not use

if you have ever had an allergic reaction to this product or any of its ingredients.

Ask a doctor before use if you have

liver or kidney disease. Your doctor should determine if you need a different dose.

When using this product

do not take more than directed. Taking more than directed may cause drowsiness.

Stop use and ask a doctor if

an allergic reaction to this product occurs. Seek medical help right away.

If pregnant or breast-feeding,

ask a health professional before use.

Keep out of reach of children.

In case of overdose, get medical help or contact a Poison Control Center right away.

Directions

adults and children 6 years and over | 1 tablet daily; not more than 1 tablet in 24 hours
children under 6 years of age | ask a doctor
consumers with liver of kidney disease | ask a doctor

Other information

- Tamper Evident: do not use if foil seal under cap is missing, open or broken.
- store between 20° to 25°C (68° to 77°F)
- protect from excessive moisture

Inactive ingredients

Corn starch, lactose monohydrate and magnesium stearate.

Questions or comments?

call 1-877-446-3679 (1-877-4-INFO-RX)

Manufactured for:
Mylan Pharmaceuticals Inc.
Morgantown, WV 26505 U.S.A.

Made in India
Code No.: MH/DRUGS/25/NKD/89

PACKAGE LABEL

PRODUCT PACKAGING

NDC 0378-8880-10

Original Prescription Strength

Non-Drowsy*

Loratadine
Tablets USP, 10 mg

Antihistamine

Indoor and Outdoor Allergies

24 Hour Relief of:

- Sneezing
- Runny Nose
- Itchy, Watery Eyes
- Itchy Throat or Nose

*When taken as directed. See Drug Facts Panel.

RMX8880C1

100 Tablets